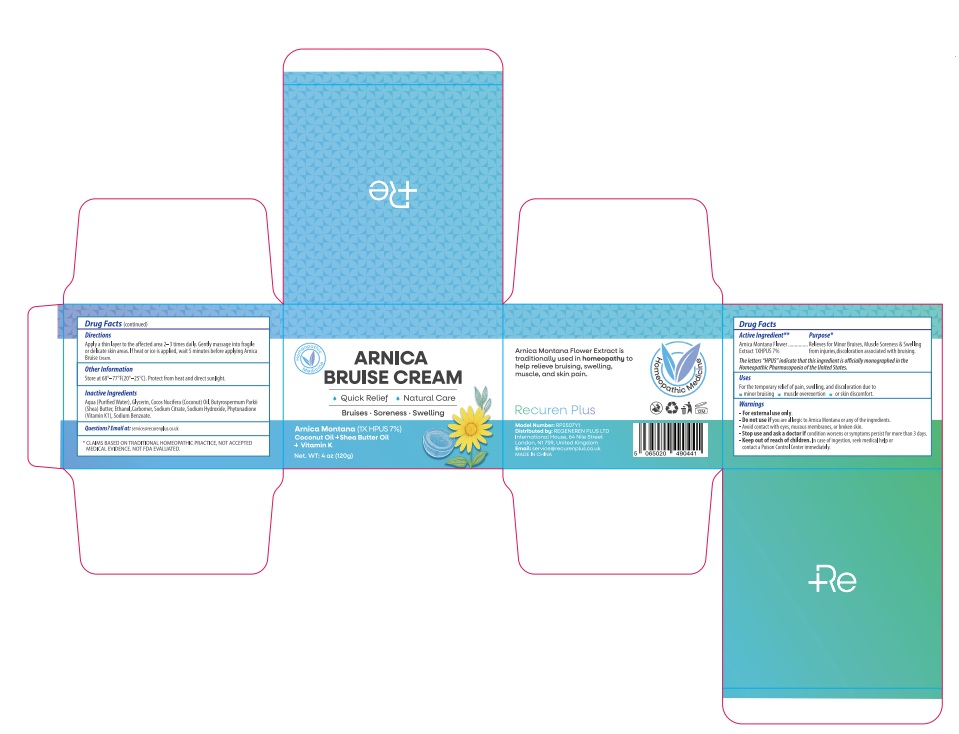 DRUG LABEL: Recuren Plus Arnica Bruise Cream
NDC: 87014-002 | Form: CREAM
Manufacturer: REGENEREN PLUS LTD
Category: homeopathic | Type: HUMAN OTC DRUG LABEL
Date: 20260212

ACTIVE INGREDIENTS: ARNICA MONTANA 7 g/100 g
INACTIVE INGREDIENTS: BUTYROSPERMUM PARKII (SHEA) BUTTER; SODIUM BENZOATE; AQUA; SODIUM CITRATE; ALCOHOL; COCOS NUCIFERA (COCONUT) OIL; SODIUM HYDROXIDE; CARBOMER; PHYTONADIONE; GLYCERIN

ACTIVE INGREDIENT

Arnica montana 1X HPUS 7%

The letters "HPUS" indicate that the components in this product are officially monographed in the Homeopathic Pharmacopoeia of the United States.

PURPOSE

Relieves for Minor Bruises, Muscle Soreness & Swelling from injuries,discoloration associated with bruising.

INDICATIONS AND USAGE

For the temporary relief of pain, swelling, and discoloration due to minor bruising, muscle overexertion, or skin discomfort.

WARNINGS

For external use only.

DO NOT USE

if you are allergic to Arnica Montana or any of the ingredients.

OTHER SAFETY INFORMATION

Avoid contact with eyes, mucous membranes, or broken skin.

Stop use and ask a doctor if condition worsens or symptoms persist for more than 3 days.

Keep out of reach of children. In case of ingestion, seek medical help or contact a Poison Control Center immediately.

DOSAGE AND ADMINISTRATION

Apply a thin layer to the affected area 2–3 times daily. Gently massage into fragile or delicate skin areas. If heat or ice is applied, wait 5 minutes before applying Arnica Bruise Cream.

STORAGE AND HANDLING

Store at 68°–77°F(20°–25°C). Protect from heat and direct sunlight.

INACTIVE INGREDIENT

Aqua (Purified Water), Glycerin, Cocos Nucifera (Coconut) Oil, Butyrospermum Parkii (Shea) Butter, Ethanol,Carbomer, Sodium Citrate, Sodium Hydroxide, Phytonadione (Vitamin K1), Sodium Benzoate.

QUESTIONS

Email at: service@recurenplus.co.uk